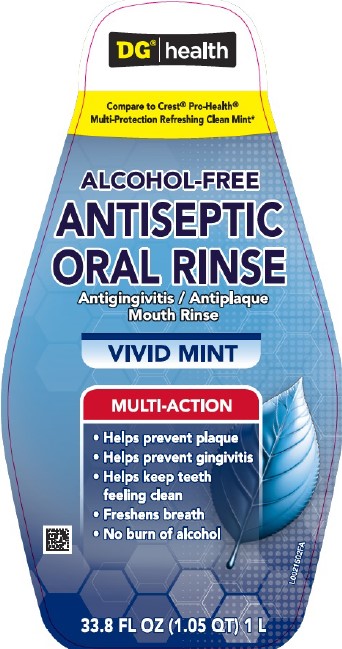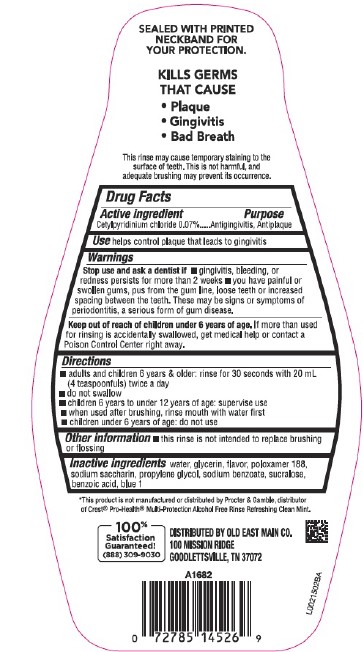 DRUG LABEL: Health
NDC: 55910-299 | Form: MOUTHWASH
Manufacturer: Old East Main Co.
Category: otc | Type: HUMAN OTC DRUG LABEL
Date: 20260302

ACTIVE INGREDIENTS: CETYLPYRIDINIUM CHLORIDE 0.7 mg/1 mL
INACTIVE INGREDIENTS: WATER; GLYCERIN; POLOXAMER 188; SACCHARIN SODIUM; PROPYLENE GLYCOL; SODIUM BENZOATE; SUCRALOSE; BENZOIC ACID; FD&C BLUE NO. 1

Dollar General 299.005/299AK-AL
Multi Action Alcohol Free Antiseptic Rinse w/CPC

Tamper Evident Statement

SEALED WITH PRINTED NECKBAND FOR YOUR PROTECTION.

Claims

KILLS GERMS THAT CAUSE

- Plaque
- Gingivitis
- Bad Breath

Disclaimer

This rinse may cause temporary staining to the surface of teeth. This is not harmful, and adequate brushing may prevent its occurrence.

Active ingredient

Cetylpyridinium chloride 0.07%

Purpose

Antigingivitis, Antiplaque

Use

helps control plaque that leads to gingivitis

Warnings

For this product

Stop Use and ask a dentist if

- gingivitis, bleeding, or redness persists for more than 2 weeks
- you have painful or swollen gums, pus from the gum line, loose teeth or increased spacing between the teeth. These may be signs or symptoms of periodontitis, a serious form of gum disease.

Keep out of reach of children under 6 years of age.

If more than used for rinsing is accidentally swallowed, get medical help or contact a Poison Control Center right away.

Directions

- adults and children 6 years & older: rinse for 30 secnds with 20 mL (4 teaspoonfuls) twice a day
- do not swallow
- children 6 years to under 12 years of age: supervise use
- when used after brushing, rinse mouth with water first
- children under 6 years of age: do not use

Other information

- this rinse is not intended to replace brushing or flossing

Inactive ingredients

water, glycerin, flavor, poloxamer 188, sodium saccharin, propylene glycol, sodium benzoate, sucralose, benzoic acid, blue 1

Disclaimer

*This product is not manufactured or distributed by Procter & Gamble, distributor of Crest®Pro-Health®Multi-Protection Alcohol Free Rinse Refreshing Clean Mint.

Adverse Reaction

DISTRIBUTED BY Old East Main Co.

100 MISSION RIDGE

GOODLETTSVILLE, TN 37072

100% Satisfaction Guaranteed!

(888)309-9030

Principal display panel

DG® health

Compare to Crest® Pro-Health® Multi-Protection Refreshing Clean Mint*

ALCOHOL-FREE

ANTISPETIC

ORAL RINSE

Antigingivitis / Antiplaque

Mouth Rinse

VIVID MINT

MULTI-ACTION

- Helps Prevent plaque
- Helps Prevent gingivitis
- Helps keep teeth feeling clean
- Freshens breath
- No burn of alcohol

33.8 FL OZ (1.05 QT) 1 L